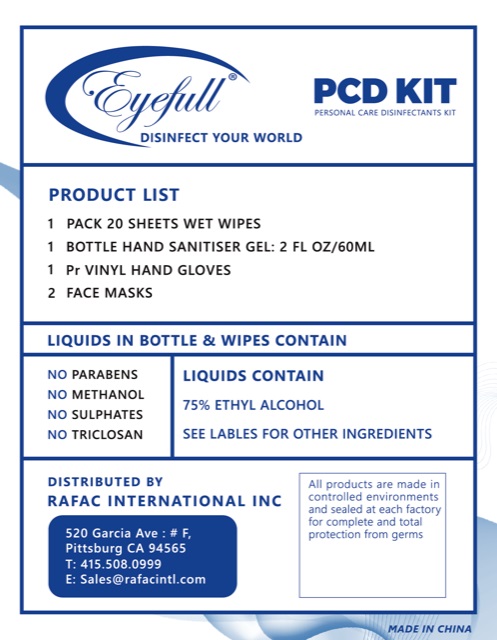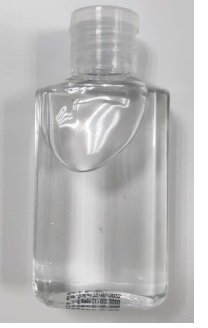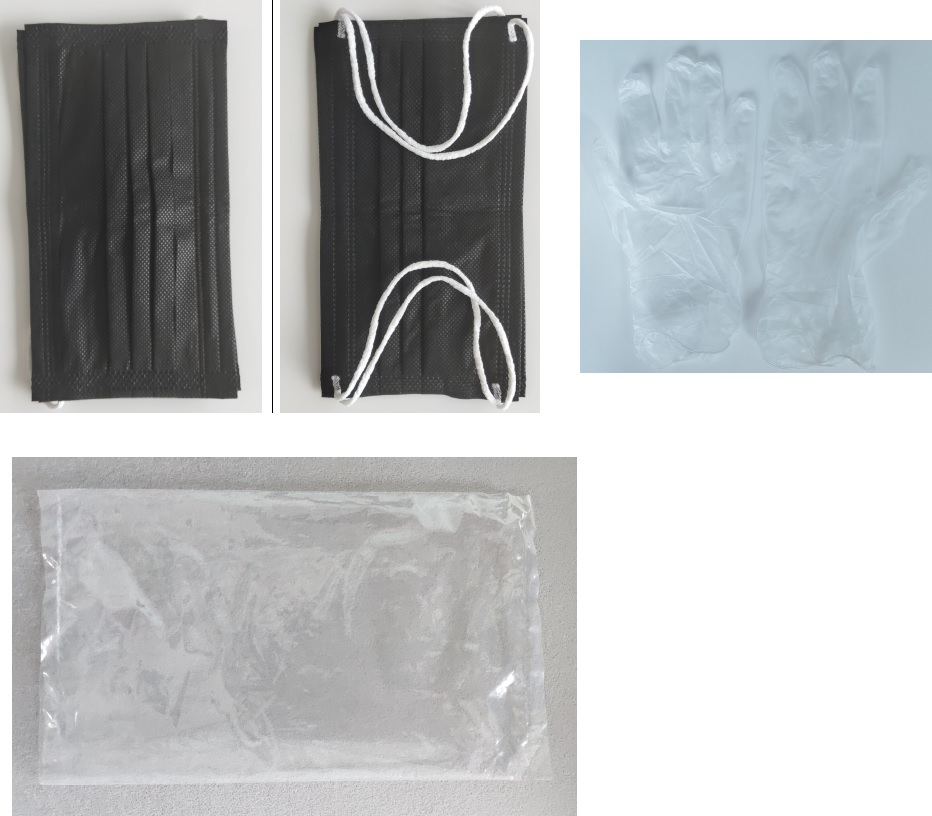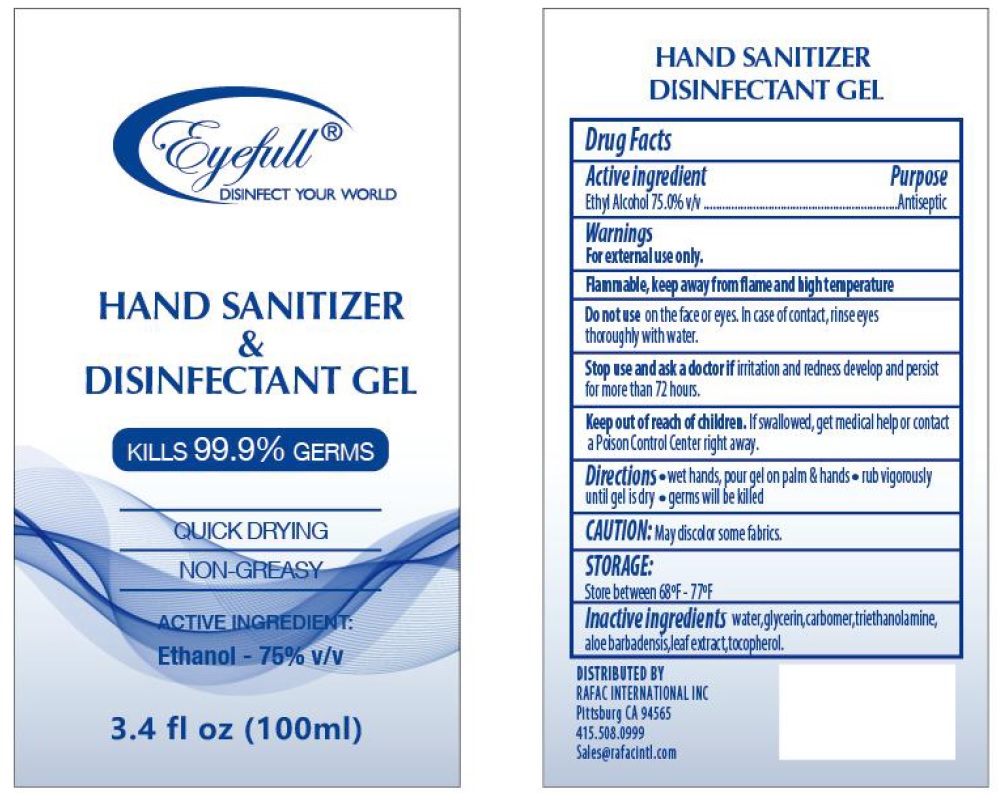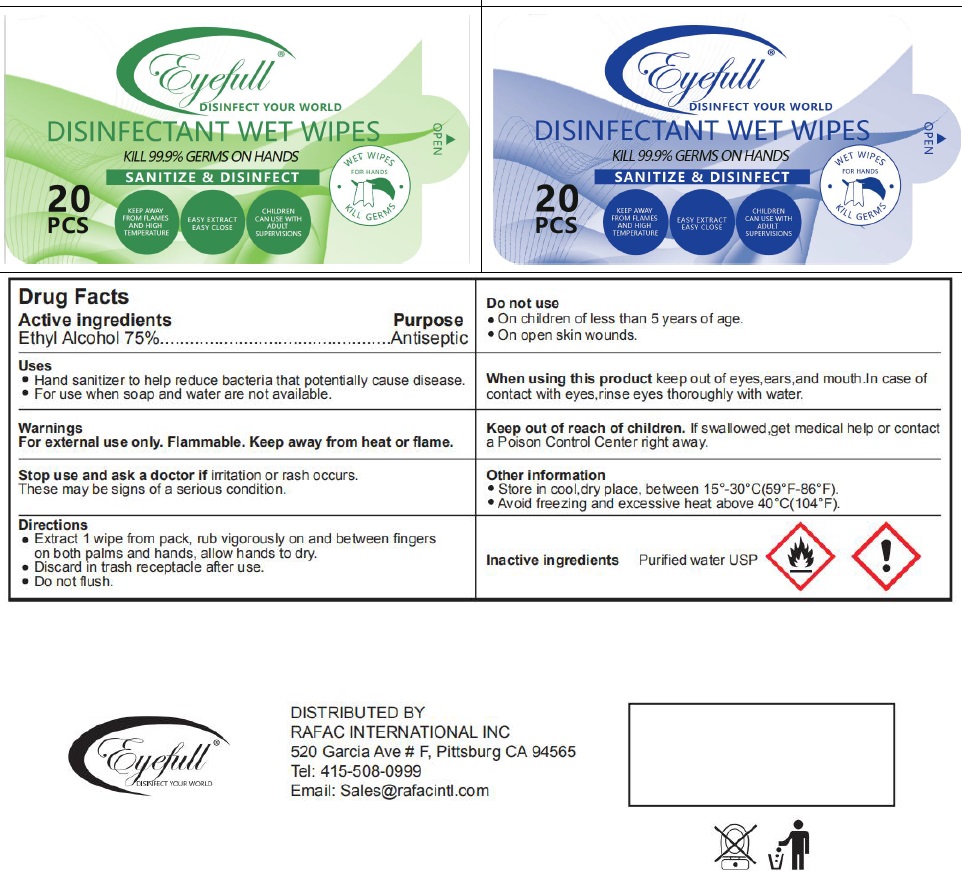 DRUG LABEL: Eyefull PCD Kit
NDC: 80184-997 | Form: KIT | Route: TOPICAL
Manufacturer: Rafac International Inc
Category: otc | Type: HUMAN OTC DRUG LABEL
Date: 20200831

ACTIVE INGREDIENTS: ALCOHOL 0.75 mL/1 mL; ALCOHOL 0.75 mL/1 mL
INACTIVE INGREDIENTS: WATER; WATER

Eyefull PCD Kit (Blue)

Active ingredients

Ethyl Alcohol 75%

Purpose

Antiseptic

Uses

- Hand sanitizer to help reduce bacteria that potentially cause disease.
- For use when soap and water are not available

Warnings

For external use only. Flammable. Keep away from heat or flame.

Stop use and ask a doctor if

irritation or rash occurs. These may be signs of a serious condition.

Do not use

- On children of less than 5 year of age.
- On open skin wounds.

When using this product

keep out of eyes,ears,and mouth.In case of contact with eyes,rinse eyes thoroughly with water.

Keep out of reach of children.

If swallowed, get medical help or contact a Poison Control Center right away

Directions

- Extract 1 wipe from pack, rub vigorously on and between fingers on both palms and hands, allow hands to dry.
- Discard in trash receptacle after use.
- Do not flush.

Other information

- Store in cool,dry place, between 15°-30°C(59°F-86°F).
- Avoid freezing and excessive heat above 40°C(104°F).

Inactive ingredients

Purified water USP